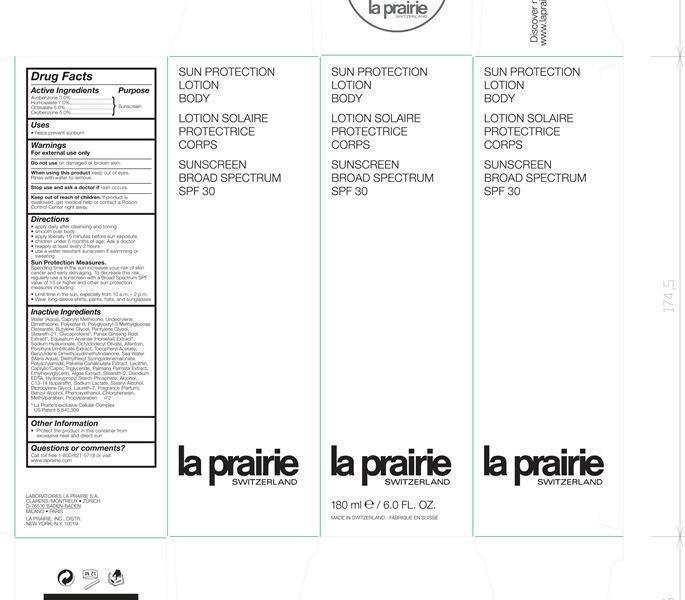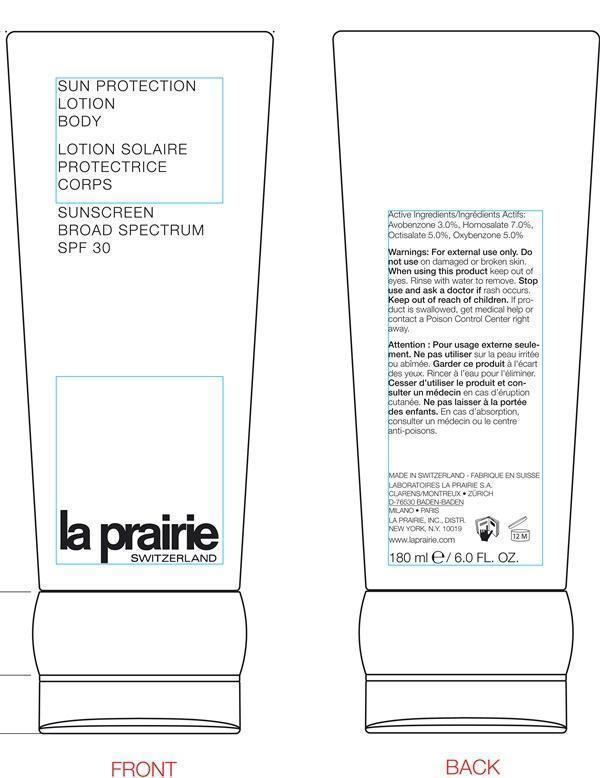 DRUG LABEL: Sun Protection Body Sunscreen Broad Spectrum SPF 30
NDC: 68807-322 | Form: LOTION
Manufacturer: Temmentec Ag
Category: otc | Type: HUMAN OTC DRUG LABEL
Date: 20160125

ACTIVE INGREDIENTS: AVOBENZONE 3.0 g/100 kg; HOMOSALATE 7.0 g/100 kg; OCTISALATE 5.0 g/100 kg; OXYBENZONE 5.0 g/100 kg
INACTIVE INGREDIENTS: WATER; CAPRYLYL TRISILOXANE; DIMETHICONE; POLYESTER-8 (1400 MW, CYANODIPHENYLPROPENOYL CAPPED); BUTYLENE GLYCOL; PENTYLENE GLYCOL; STEARETH-21; ASIAN GINSENG; HYALURONATE SODIUM; ALLANTOIN; PORPHYRA UMBILICALIS; .ALPHA.-TOCOPHEROL ACETATE; BENZYLIDENE DIMETHOXYDIMETHYLINDANONE; SODIUM CHLORIDE; DIETHYLHEXYL SYRINGYLIDENEMALONATE; POLYACRYLAMIDE (1500 MW); PELVETIA CANALICULATA; LECITHIN, SOYBEAN; MEDIUM-CHAIN TRIGLYCERIDES; DULSE; ETHYLHEXYLGLYCERIN; STEARETH-2; EDETATE DISODIUM; ALCOHOL; C13-14 ISOPARAFFIN; SODIUM LACTATE; STEARYL ALCOHOL; DIPROPYLENE GLYCOL; LAURETH-7; BENZYL ALCOHOL; PHENOXYETHANOL; CHLORPHENESIN; METHYLPARABEN; PROPYLPARABEN

Sun Protection Lotion Body Sunscreen SPf 30

Active Ingredients Purpose

Avobenzone 3.0% Sunscreen

Homosalate 7.0 % Sunscreen

Octisalate 5.0% Sunscreen

Oxybenzone 5.0% Sunscreen

Uses

helps prevent sunburn

warning

Keep out of reach of children. If product is swallowed, get medical help or contact a Poison Control Center right away

indications

Stop use and ask a doctor if rash occurs.

warnings

For external use only.

Do not use on damaged or broken skin.

When using this product keep out of eyes.

Rinse with water to remove.

Directions

apply daily after cleansing and toning

smooth over body

apply liberally 15 minutes before sun exposure

children under 6 months of age: Ask a doctor

reapply at least every 2 hours

use a water resistant sunscreen if swimming or sweating

Sun Protection Measures. Spending time in the sun increases your risk of skin cancer and early skin aging. To decrease this risk, regularly use a sunscreen with a Broad Spectrum SPF value of 15 or higher and other sun protection measures including:

Limit time in the sun, especially from 10 a.m. – 2 p.m.

Wear long-sleeve shirts, pants, hats, and sunglasses

Inactive ingredients

Water (Aqua), Caprylyl Methicone, Undecrylene Dimethicone, Polyester-8, Polyglyceryl-3 Methylglucose Distearate, Butylene Glycol, Pentylene Glycol, Steareth-21, Glycoproteins, Panax Ginseng Root Extract, Equisetum Arvense (Horsetail) Extract, Sodium Hyaluronate, Octyldodecyl Olivate, Allantoin, Porphyra Umbilicalis Extract, Tocopheryl Acetate, Benzylidene Dimethoxydimethylindanone, Sea Water (Maris Aqua), Diethylhexyl Syringyldenemalonate, Polyacrylamide, Pelvetia Canaliculata Extract, Lecithin, Caprylic/Capric Triglyceride, Palmaria Palmata Extract, Ethylhexylglycerin, Algae Extract, Steareth-2, Disodium EDTA, Hydroxypropyl Starch Phosphate, Alcohol, C13-14 Isoparaffin, Sodium Lactate, Stearyl Alcohol, Dipropylene Glycol, Laureth-7, Fragrance (Parfum), Benzyl Alcohol, Phenoxyethanol, Chlorphenesin, Methylparaben, Propylparaben

display panel

Sun Protection Lotion Body

Lotion Solaire Protectrice Corps

Sunscreen Broad Spectrum SPF 30

La Prairie Switzerland

180 ml/ 6.0 Fl. Oz.

Made in Switzerland - Fabrique en Suisse